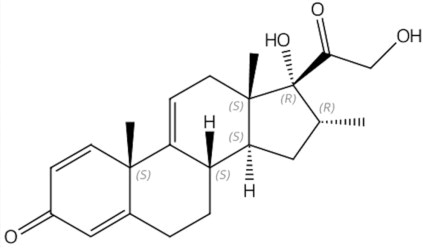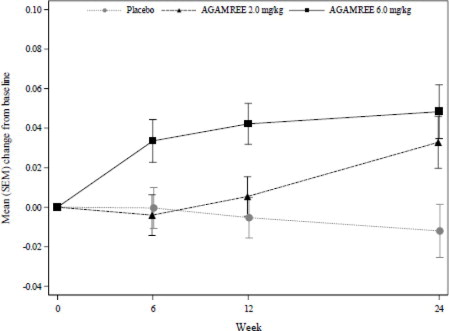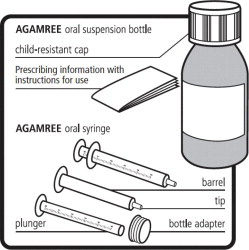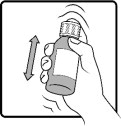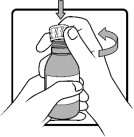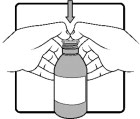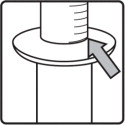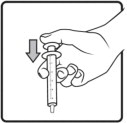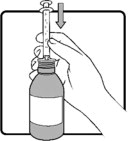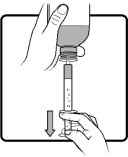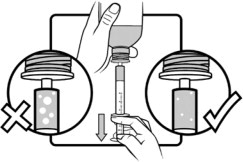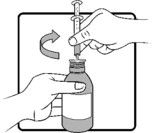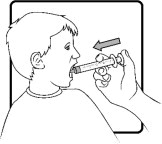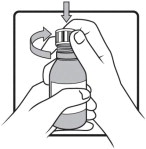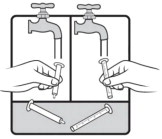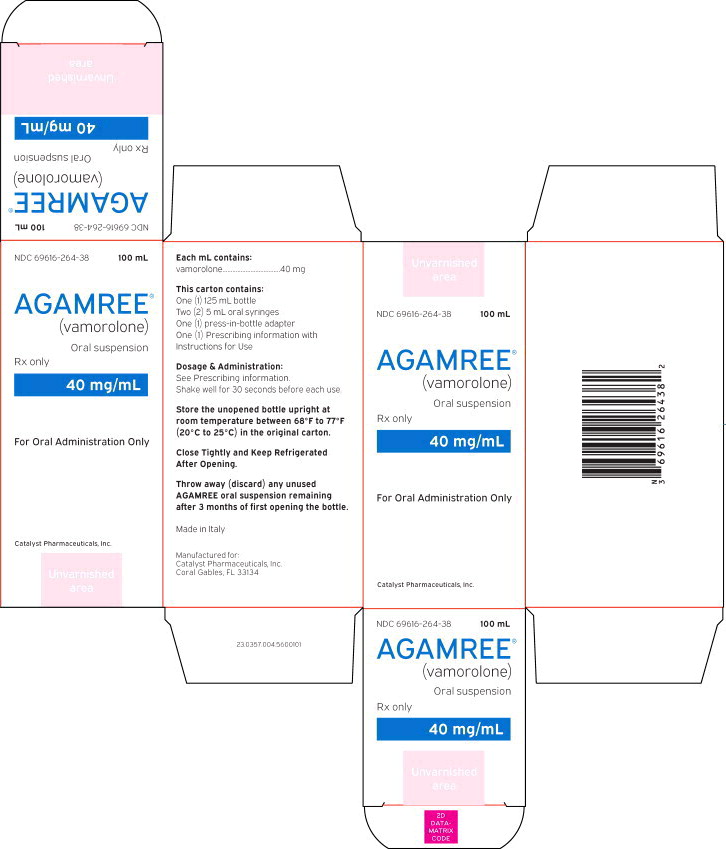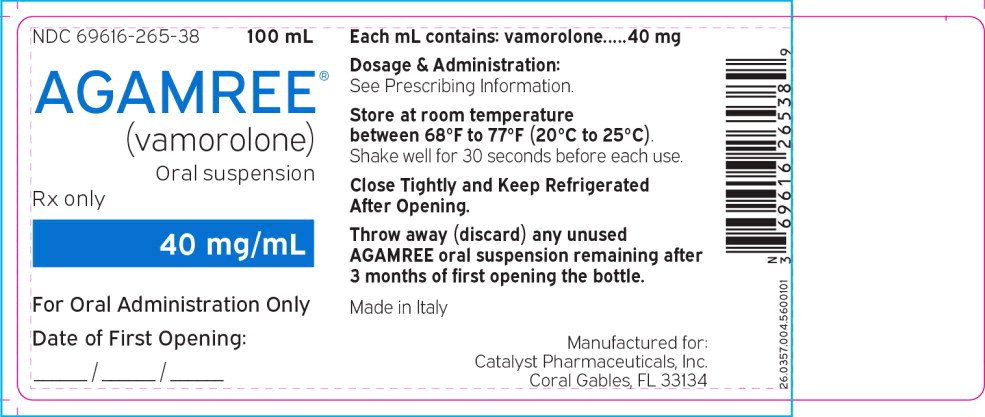 DRUG LABEL: AGAMREE
NDC: 69616-264 | Form: KIT | Route: ORAL
Manufacturer: Catalyst Pharmaceuticals, Inc.
Category: prescription | Type: HUMAN PRESCRIPTION DRUG LABEL
Date: 20260122

ACTIVE INGREDIENTS: VAMOROLONE 40 mg/1 mL
INACTIVE INGREDIENTS: SUCRALOSE; XANTHAN GUM; SODIUM PHOSPHATE, DIBASIC, ANHYDROUS; CITRIC ACID MONOHYDRATE; SODIUM BENZOATE; GLYCERIN; HYDROCHLORIC ACID; WATER

HIGHLIGHTS OF PRESCRIBING INFORMATION

These highlights do not include all the information needed to use AGAMREE®safely and effectively. See full prescribing information for AGAMREE.
AGAMREE (vamorolone) oral suspension
Initial U.S. Approval: 2023

RECENT MAJOR CHANGES

Warnings and Precautions,
Immunosuppression and Increased Risk of Infection (5.2) | 06/2024

1 INDICATIONS AND USAGE

AGAMREE is a corticosteroid indicated for the treatment of Duchenne muscular dystrophy (DMD) in patients 2 years of age and older. (1)

2 DOSAGE AND ADMINISTRATION

- The recommended dosage is 6 mg/kg taken orally once daily preferably with a meal, up to a maximum daily dosage of 300 mg for patients weighing more than 50 kg. (2.2)
- In patients with mild to moderate hepatic impairment, the recommended dosage is 2 mg/kg taken orally once daily preferably with a meal, up to a maximum daily dosage of 100 mg for patients weighing more than 50 kg. (2.3)
- Decrease dosage gradually when administered for more than one week. (2.7)

3 DOSAGE FORMS AND STRENGTHS

Oral Suspension: 40 mg/mL (3)

4 CONTRAINDICATIONS

Hypersensitivity to vamorolone or any of the inactive ingredients in AGAMREE (4)

5 WARNINGS AND PRECAUTIONS

- Alterations in Endocrine Function:Hypothalamic-pituitary-adrenal axis suppression, cushingoid features, and hyperglycemia can occur. Monitor patients for these conditions with chronic use of AGAMREE. (2.7, 5.1)
- Immunosuppression and Increased Risk of Infection:Increased risk of new infections, exacerbation, dissemination, or reactivation of latent infections, which can be severe and at times fatal; signs and symptoms of infections may be masked. (5.2)
- Alterations in Cardiovascular/Renal Function:Monitor for elevated blood pressure and monitor sodium and potassium levels in patients chronically treated with AGAMREE. (5.3)
- Gastrointestinal Perforation:Increased risk in patients with certain GI disorders; signs and symptoms may be masked. (5.4)
- Behavioral and Mood Disturbances:May include euphoria, insomnia, mood swings, personality changes, severe depression, and psychosis. (5.5)
- Effects on Bones:Monitor for decreases in bone mineral density with chronic use of AGAMREE. (5.6)
- Ophthalmic Effects:May include cataracts, infections, and glaucoma; monitor intraocular pressure in patients chronically treated with AGAMREE. (5.7)
- Vaccination:Do not administer live or live attenuated vaccines to patients receiving immunosuppressive doses of corticosteroids. Administer live-attenuated or live vaccines at least 4 to 6 weeks prior to starting AGAMREE. (5.8)

6 ADVERSE REACTIONS

The most common adverse reactions (>10% for AGAMREE and greater than placebo) are cushingoid features, psychiatric disorders, vomiting, weight increased, and vitamin D deficiency. (6.1)

To report SUSPECTED ADVERSE REACTIONS, contact Catalyst Pharmaceuticals, Inc. at 1-844-347-3277 or FDA at 1-800-FDA-1088 or www.fda.gov/medwatch.

7 DRUG INTERACTIONS

- Strong CYP3A4 inhibitors: The maximum recommended daily dose is 4 mg/kg up to a maximum daily dosage of 200 mg for patients weighing more than 50 kg. (2.6, 7.1)

FULL PRESCRIBING INFORMATION

1 INDICATIONS AND USAGE

AGAMREE is indicated for the treatment of Duchenne muscular dystrophy (DMD) in patients 2 years of age and older.

2 DOSAGE AND ADMINISTRATION

2.1 Assessments Prior to First Dose of AGAMREE

Administer all immunizations according to immunization guidelines prior to starting AGAMREE. Administer live-attenuated or live vaccines at least 4 to 6 weeks prior to starting AGAMREE [see Warnings and Precautions (5.8)].

2.2 Dosing Information

The recommended dosage of AGAMREE is 6 mg/kg taken orally once daily preferably with a meal, up to a maximum daily dosage of 300 mg for patients weighing more than 50 kg.

Some patients may respond to a dose of 2 mg/kg daily. Doses may be titrated down to 2 mg/kg/day as needed, based on individual tolerability.

2.3 Recommended Dosage for Hepatic Impairment

The recommended dosage of AGAMREE in patients with mild (Child-Pugh A) to moderate (Child-Pugh B) hepatic impairment is 2 mg/kg taken orally once daily preferably with a meal, up to a maximum daily dosage of 100 mg for patients weighing more than 50 kg [see Use in Specific Populations (8.6) and Clinical Pharmacology (12.3)] .

Doses may be titrated down based on individual tolerability.

2.4 Important Preparation and Administration Instructions

Shake AGAMREE oral suspension well for about 30 seconds before administration.

Use only the oral syringe provided with the product. After withdrawing the appropriate dose into the oral syringe, dispense directly into the mouth.

Discard any unused AGAMREE oral suspension remaining after 3 months of first opening the bottle.

2.5 Switching from Corticosteroid Treatment to AGAMREE

Patients can be switched from oral corticosteroid treatment (such as prednisone or deflazacort) to AGAMREE without treatment interruption or period of prior corticosteroid dosage reduction to minimize the risk for adrenal insufficiency.

Patients switching after long-term treatment with oral corticosteroids should start AGAMREE at a dosage of 6 mg/kg/day.

2.6 Dosage Modification for Use with Strong CYP3A4 Inhibitors

The recommended dosage of AGAMREE when administered with strong CYP3A4 inhibitors is 4 mg/kg taken orally once daily preferably with a meal, up to a maximum daily dosage of 200 mg for patients weighing more than 50 kg [see Drug Interactions (7.1) and Clinical Pharmacology (12.3)].

Doses may be titrated down based on individual tolerability.

2.7 Discontinuation

Dosage of AGAMREE must be decreased gradually if the drug has been administered for more than one week [see Warnings and Precautions (5.1)].

3 DOSAGE FORMS AND STRENGTHS

Oral Suspension: 40 mg/mL orange flavored white to off-white suspension

4 CONTRAINDICATIONS

AGAMREE is contraindicated in patients with known hypersensitivity to vamorolone or to any of the inactive ingredients of AGAMREE. Instances of hypersensitivity, including anaphylaxis, have occurred in patients receiving corticosteroid therapy [see Warnings and Precautions (5.13)].

5 WARNINGS AND PRECAUTIONS

5.1 Alterations in Endocrine Function

Corticosteroids, such as AGAMREE, can cause serious and life-threatening alterations in endocrine function, especially with chronic use. Monitor patients receiving AGAMREE for Cushing's syndrome, hyperglycemia, and adrenal insufficiency after AGAMREE withdrawal. In addition, patients with hypopituitarism, primary adrenal insufficiency or congenital adrenal hyperplasia, altered thyroid function, or pheochromocytoma may be at increased risk for adverse endocrine events.

Risk of Adrenal Insufficiency Following Withdrawal

AGAMREE produces reversible hypothalamic-pituitary-adrenal (HPA) axis suppression, with the potential for the development of secondary adrenal insufficiency after withdrawal. Acute adrenal insufficiency can occur if AGAMREE is withdrawn abruptly, and could be fatal. The degree and duration of adrenocortical insufficiency produced is variable among patients and depends on the dose and duration of therapy.

The risk of adrenal insufficiency is reduced by gradually tapering the dose when withdrawing treatment. The insufficiency may persist, however, for months after discontinuation of prolonged therapy; therefore, in any situation of stress occurring during that period of discontinuation, supplementation with a systemic corticosteroid is recommended. For patients already taking corticosteroids during times of stress, the dosage may need to be increased.

A steroid “withdrawal syndrome”, seemingly unrelated to adrenocortical insufficiency, may also occur following abrupt discontinuance of corticosteroids. This syndrome includes symptoms such as anorexia, nausea, vomiting, lethargy, headache, fever, joint pain, desquamation, myalgia, and/or weight loss. These effects are thought to be due to the sudden change in corticosteroid concentration rather than too low corticosteroid levels.

Cushing's Syndrome

Cushing's syndrome (hypercortisolism) occurs with prolonged exposure to exogenous corticosteroids, including AGAMREE, and symptoms include hypertension, truncal obesity and thinning of the limbs, purple striae, facial rounding, facial plethora, muscle weakness, easy and frequent bruising with thin fragile skin, posterior neck fat deposition, osteopenia, acne, amenorrhea, hirsutism, and psychiatric abnormalities.

Hyperglycemia

Corticosteroids can increase blood glucose, worsen pre-existing diabetes, predispose those on long-term therapy to diabetes mellitus, and may reduce the effect of anti-diabetic drugs.

Monitor blood glucose at regular intervals in patients treated with AGAMREE. For patients with hyperglycemia, anti-diabetic treatment should be initiated or adjusted accordingly.

Considerations for Use in Patients with Altered Thyroid Function

Metabolic clearance of corticosteroids is decreased in hypothyroid patients and increased in hyperthyroid patients. Changes in thyroid status of the patient may necessitate a dose adjustment of the corticosteroid. When concomitant administration of AGAMREE and levothyroxine is required, administration of AGAMREE should precede the initiation of levothyroxine therapy to reduce the risk of adrenal crisis.

Pheochromocytoma Crisis

There have been reports of pheochromocytoma crisis, which can be fatal, after administration of systemic corticosteroids. In patients with suspected or identified pheochromocytoma, consider the risk of pheochromocytoma crisis prior to administering corticosteroids.

5.2 Immunosuppression and Increased Risk of Infection

Corticosteroids, including AGAMREE, suppress the immune system and increase the risk of infection with any pathogen, including viral, bacterial, fungal, protozoan, or helminthic pathogens.

Corticosteroids can:

- reduce resistance to new infections
- exacerbate existing infections
- increase the risk of disseminated infections
- increase the risk of reactivation or exacerbation of latent infections
- mask some signs of infection

Corticosteroid-associated infections can be mild but can be severe, and at times fatal. The rate of infectious complications increases with increasing corticosteroid dosages.

Monitor for the development of infection and consider AGAMREE withdrawal or dosage reduction as needed.

Tuberculosis

If AGAMREE is used to treat a condition in patients with latent tuberculosis or tuberculin reactivity, reactivation of tuberculosis may occur. Closely monitor such patients for reactivation. During prolonged AGAMREE therapy, patients with latent tuberculosis or tuberculin reactivity should receive chemoprophylaxis.

Varicella Zoster and Measles Viral Infections

Varicella and measles can have a serious or even fatal course in non-immune patients taking corticosteroids, including AGAMREE. In corticosteroid-treated patients who have not had these diseases or are non-immune, particular care should be taken to avoid exposure to varicella and measles.

- If an AGAMREE-treated patient is exposed to varicella, prophylaxis with varicella zoster immunoglobulin may be indicated. If varicella develops, treatment with antiviral agents may be considered.
- If an AGAMREE-treated patient is exposed to measles, prophylaxis with immunoglobulin may be indicated.

Hepatitis B Virus Reactivation

Hepatitis B virus reactivation can occur in patients who are hepatitis B carriers treated with immunosuppressive dosages of corticosteroids, including AGAMREE. Reactivation can also occur infrequently in corticosteroid-treated patients who appear to have resolved hepatitis B infection.

Screen patients for hepatitis B infection before initiating immunosuppressive (e.g., prolonged) treatment with AGAMREE. For patients who show evidence of hepatitis B infection, recommend consultation with physicians with expertise in managing hepatitis B regarding monitoring and consideration for hepatitis B antiviral therapy.

Fungal Infections

Corticosteroids, including AGAMREE, may exacerbate systemic fungal infections; therefore, avoid AGAMREE use in the presence of such infections unless AGAMREE is needed to control drug reactions. For patients on chronic AGAMREE therapy who develop systemic fungal infections, AGAMREE withdrawal or dosage reduction is recommended.

Amebiasis

Corticosteroids, including AGAMREE, may activate latent amebiasis. Therefore, it is recommended that latent amebiasis or active amebiasis be ruled out before initiating AGAMREE in any patients who have spent time in the tropics or patients with unexplained diarrhea.

Strongyloides Infestation

Corticosteroids, including AGAMREE, should be used with great care in patients with known or suspected Strongyloides (threadworm) infestation. In such patients, corticosteroid-induced immunosuppression may lead to Strongyloides hyperinfection and dissemination with widespread larval migration, often accompanied by severe enterocolitis and potentially fatal gram-negative septicemia.

Cerebral Malaria

Avoid corticosteroids, including AGAMREE, in patients with cerebral malaria.

5.3 Alterations in Cardiovascular/Renal Function

Corticosteroids, including AGAMREE, can cause elevation of blood pressure, salt and water retention, and increased excretion of potassium and calcium.

Monitor blood pressure and assess for signs and symptoms of volume overload. Monitor serum potassium levels.

AGAMREE should be used with caution in patients with congestive heart failure, hypertension, or renal insufficiency. Literature reports suggest an association between use of corticosteroids and left free wall rupture after a recent myocardial infarction; therefore, therapy with AGAMREE should be used with great caution in these patients.

5.4 Gastrointestinal Perforation

There is an increased risk of gastrointestinal perforation with use of corticosteroids in patients with certain gastrointestinal disorders, such as active or latent peptic ulcers, diverticulitis, fresh intestinal anastomoses, and non-specific ulcerative colitis. Signs of gastrointestinal perforation, such as peritoneal irritation, may be masked in patients receiving corticosteroids.

Avoid AGAMREE if there is a probability of impending perforation, abscess, or other pyogenic infections; diverticulitis; fresh intestinal anastomoses; or active or latent peptic ulcer.

5.5 Behavioral and Mood Disturbances

Potentially severe psychiatric adverse reactions may occur with systemic corticosteroids, including AGAMREE. Symptoms typically emerge within a few days or weeks of starting treatment and may be dose-related. These reactions may improve after either dose reduction or withdrawal, although pharmacologic treatment may be necessary.

In Study 1, psychiatric adverse reactions were reported in 21% of patients on AGAMREE 6 mg/kg, 10% of patients on AGAMREE 2 mg/kg, and 14% of patients on placebo. Psychiatric adverse reactions reported on AGAMREE resolved without requiring treatment or drug discontinuation.

In adults, psychiatric adverse reactions with corticosteroids usually involve hypomanic or manic symptoms (e.g., euphoria, insomnia, mood swings) during treatment and depressive episodes after discontinuation of treatment. In children receiving corticosteroids, psychiatric adverse reactions usually involve hyperactivity symptoms (e.g., irritability, aggressive behavior, increased frequency of tantrums, and mood swings) and sleep disorder during treatment. Inform patients or caregivers of the potential for behavioral and mood changes and encourage them to seek medical attention if psychiatric symptoms develop, especially if depressed mood or suicidal ideation is suspected.

5.6 Effects on Bones

Decreased Bone Mineral Density

Corticosteroids, such as AGAMREE, decrease bone formation and increase bone resorption both through their effect on calcium regulation (i.e., decreasing absorption and increasing excretion) and inhibition of osteoblast function. This, together with a decrease in the protein matrix of the bone secondary to an increase in protein catabolism and reduced sex hormone production, may lead to inhibition of bone growth in pediatric patients and the development of bone loss at any age. Bone loss can predispose patients to vertebral and long bone fractures.

Consider a patient's risk of osteoporosis before initiating corticosteroid therapy. Monitor bone mineral density in patients on long-term treatment with AGAMREE.

Avascular Necrosis

Corticosteroids may cause avascular necrosis.

5.7 Ophthalmic Effects

The use of corticosteroids, such as AGAMREE, may produce posterior subcapsular cataracts. Corticosteroids may also cause glaucoma with possible damage to the optic nerves, and may increase the risk of secondary ocular infections caused by bacteria, fungi, or viruses. Corticosteroids are not recommended for patients with active ocular herpes simplex. Intraocular pressure may become elevated in some patients taking corticosteroids. If treatment with AGAMREE is continued for more than 6 weeks, monitor intraocular pressure.

5.8 Immunizations

Administer all immunizations according to immunization guidelines prior to starting AGAMREE. Administer live-attenuated or live vaccines at least 4 to 6 weeks prior to starting AGAMREE. Patients on AGAMREE may receive concurrent vaccinations, except for live-attenuated or live vaccines.

5.9 Effects on Growth and Development

Long-term use of corticosteroids, including AGAMREE, can have negative effects on growth and development in children.

5.10 Myopathy

Patients receiving corticosteroids and concomitant therapy with neuromuscular blocking agents (e.g., pancuronium) or patients with disorders of neuromuscular transmission (e.g., myasthenia gravis) may be at increased risk of developing acute myopathy. This acute myopathy is generalized, may involve ocular and respiratory muscles, and may result in quadriparesis. Clinical improvement or recovery after stopping corticosteroids may require weeks to years.

5.11 Kaposi's Sarcoma

Kaposi's sarcoma has been reported to occur in patients receiving corticosteroid therapy, most often for chronic conditions. Discontinuation of corticosteroids may result in clinical improvement of Kaposi's sarcoma.

5.12 Thromboembolic Events

Observational studies have shown an increased risk of thromboembolism (including venous thromboembolism) particularly with higher cumulative doses of corticosteroids. It is unclear if risk differs by daily dose or duration of use. Use AGAMREE with caution in patients who have or may be predisposed to thromboembolic disorders.

5.13 Anaphylaxis

Rare instances of anaphylaxis have occurred in patients receiving corticosteroid therapy.

6 ADVERSE REACTIONS

The following serious adverse reactions are discussed in more detail in other sections:

- Alterations in Endocrine Function [see Warnings and Precautions (5.1)]
- Immunosuppression and Increased Risk of Infection [see Warnings and Precautions (5.2)]
- Alterations in Cardiovascular/Renal Function [see Warnings and Precautions (5.3)]
- Gastrointestinal Perforation [see Warnings and Precautions (5.4)]
- Behavioral and Mood Disturbances [see Warnings and Precautions (5.5)]
- Effects on Bones [see Warnings and Precautions (5.6)]
- Ophthalmic Effects [see Warnings and Precautions (5.7)]
- Immunizations [see Warnings and Precautions (5.8)]
- Effects on Growth and Development [see Warnings and Precautions (5.9)]
- Myopathy [see Warnings and Precautions (5.10)]
- Kaposi's Sarcoma [see Warnings and Precautions (5.11)]
- Thromboembolic Events [see Warnings and Precautions (5.12)]
- Anaphylaxis [see Warnings and Precautions (5.13)]

6.1 Clinical Trials Experience

Because clinical trials are conducted under widely varying conditions, adverse reaction rates observed in the clinical trials of a drug cannot be directly compared to rates in the clinical trials of another drug and may not reflect the rates observed in practice.

Common Adverse Reactions in Clinical Studies

Table 1lists the adverse reactions that occurred in ≥ 5% of the patients treated with AGAMREE 6 mg/kg/day (N=28) or AGAMREE 2 mg/kg/day (N=30) and that occurred more frequently than in the patients who received placebo (N=29) in Study 1 [see Clinical Studies (14)] , which was 24 weeks and included patients with DMD between the ages of 4 and 7 years.

Table 1: Adverse Reactions in Patients with DMD that Occurred in ≥ 5% of Patients Treated with AGAMREE and More Frequently than in Patients Who Received Placebo During 24 Weeks (Study 1)
Adverse Reaction | AGAMREE 2 mg/kg/d (N=30) % | AGAMREE 6 mg/kg/d (N=28) % | Placebo (N=29) %
Cushingoid Features | 7 | 29 | 0
Psychiatric disorders^1 | 7 | 21 | 14
Vomiting | 17 | 14 | 7
Weight increased | 0 | 11 | 3
Vitamin D deficiency | 7 | 11 | 0
Cough | 10 | 7 | 3
Headache | 7 | 7 | 3
Diarrhea | 3 | 7 | 3
Increased appetite | 3 | 7 | 3
Rhinitis | 3 | 7 | 3
^1Includes the following adverse reactions that occurred more frequently in the AGAMREE group than in placebo: abnormal behavior, aggression, agitation, anxiety, irritability, mood altered, sleep disorder, and stereotypy.

In a separate open-label safety study of pediatric patients aged 2 to less than 4 years (n=16) and pediatric patients aged 7 to less than 18 years (n=16) with DMD, adverse reactions were similar to those seen in the Study 1 pediatric patients.

7 DRUG INTERACTIONS

7.1 Effect of Other Drugs on Vamorolone

Co-administration of AGAMREE with itraconazole, a strong CYP3A4 inhibitor, increases vamorolone exposure [see Clinical Pharmacology (12.3)] . Reduce the dosage of AGAMREE in patients when strong CYP3A4 inhibitors are used concomitantly [see Dosage and Administration (2.6)] . No dosage adjustments are required when AGAMREE is concomitantly administered with moderate or weak CYP3A4 inhibitors.

8 USE IN SPECIFIC POPULATIONS

8.1 Pregnancy

Risk Summary

AGAMREE is indicated for use for the treatment of DMD, which is a disease of young male patients. However, corticosteroids in general should be used during pregnancy only if the potential benefit justifies the potential risk to the fetus. Infants born to mothers who have received substantial doses of corticosteroids during pregnancy should be carefully observed for signs of hypoadrenalism. There are no data on the use of AGAMREE during pregnancy.

Adverse developmental outcomes, including orofacial clefts (cleft lip, with or without cleft palate) and intrauterine growth restriction, and decreased birth weight, have been reported with maternal use of corticosteroids during pregnancy. Some epidemiologic studies report an increased risk of orofacial clefts from about 1 per 1000 infants to 3 to 5 per 1000 infants; however, a risk for orofacial clefts has not been observed in all clinical studies. Intrauterine growth restriction and decreased birth weight appear to be dose-related; however, the underlying maternal condition may also contribute to these risks (see Clinical Considerationsand Data) .

Animal reproduction studies have not been conducted with AGAMREE.

Animal reproduction studies conducted with corticosteroids in pregnant mice, rats, hamsters, and rabbits using clinically relevant doses have shown an increased incidence of cleft palate. An increase in embryofetal death, intrauterine growth retardation, and constriction of the ductus arteriosus were observed in some animal species.

In the U.S. general population, the estimated background risk of major birth defects and miscarriage in clinically recognized pregnancies is 2-4% and 15-20%, respectively.

Clinical Considerations

Fetal/Neonatal Adverse Reactions

Hypoadrenalism may occur in infants born to mothers receiving corticosteroids during pregnancy. Infants should be carefully observed for signs of hypoadrenalism, such as poor feeding, irritability, weakness, and vomiting, and managed accordingly [see Warnings and Precautions (5.1)].

Data

Human Data

Multiple cohort and case-controlled studies in humans suggest that maternal corticosteroid use during the first trimester increases the rate of cleft lip, with or without cleft palate, from about 1/1000 infants to 3-5/1000 infants. Two prospective case-controlled studies showed decreased birth weight in infants exposed to maternal corticosteroids in utero.

8.2 Lactation

Risk Summary

There are no data on the presence of vamorolone in human milk or the effects on milk production.

AGAMREE is indicated for use for the treatment of DMD, which is a disease of young male patients. However, systemically administered corticosteroids appear in human milk and could suppress growth, interfere with endogenous corticosteroid production, or cause other untoward effects. The developmental and health benefits of breastfeeding should be considered along with the mother's clinical need and any potential adverse effects on the breastfed infant.

8.4 Pediatric Use

The safety and effectiveness of AGAMREE for the treatment of DMD have been established in patients 2 years of age and older. Use of AGAMREE in pediatric patients is supported by a multicenter, randomized, double-blind, placebo- and active-controlled study in 121 males 4 to less than 7 years of age [see Clinical Studies (14)]. Use of AGAMREE in patients 2 years to less than 4 years of age and 7 to less than 18 years of age is supported by findings of efficacy and safety in patients 4 to less than 7 years of age with DMD, and by pharmacokinetic and safety data from patients 2 to 4 years of age and 7 to less than 18 years of age [see Adverse Reactions (6.1) and Clinical Pharmacology (12.3)] .

The safety and effectiveness in pediatric patients below the age of 2 years have not been established.

Juvenile Animal Toxicity Data

Oral administration of vamorolone (0, 15, 30, or 100 mg/kg/day) to juvenile mice from postnatal days 21 to 81 resulted in no adverse effects on neurobehavioral function, sexual maturation, or reproductive function. Atrophy of the adrenal cortex, degeneration/necrosis of the liver, and decreased lymphocytes in lymphatic tissues were observed at all doses. A no-effect dose for general toxicity was not identified. Plasma exposures (AUC) at the lowest dose tested (15 mg/kg/day) were lower than that in humans at the maximum recommended human dose (300 mg/day).

8.5 Geriatric Use

DMD is largely a disease of children and young adults; therefore, there is no geriatric experience with AGAMREE.

8.6 Hepatic Impairment

Moderate hepatic impairment increases vamorolone exposure [see Clinical Pharmacology (12.3)]. Reduce the AGAMREE dosage in patients with mild to moderate hepatic impairment [see Dosage and Administration (2.3)]. There is no clinical experience with AGAMREE in patients with severe hepatic impairment, and a dosing recommendation cannot be provided for patients with severe hepatic impairment.

10 OVERDOSAGE

Treatment of acute overdosage of vamorolone is by immediate supportive and symptomatic therapy. Gastric lavage or emesis can be considered.

11 DESCRIPTION

AGAMREE (vamorolone) oral suspension contains vamorolone, a corticosteroid. Vamorolone [17α,21-dihydroxy-16α-methyl-pregna-1,4,9(11)-triene-3,20-dione] is a white to off-white powder with a molecular formula of C22H28O4and a molecular weight of 356.46 g/mol. Its structural formula is:

Vamorolone is freely soluble in methanol and dioxane and sparingly soluble in ethanol and acetone.

AGAMREE for oral administration is available as an oral suspension in a strength of 40 mg/mL. The oral suspension contains vamorolone and the following inactive ingredients: citric acid (monohydrate), disodium phosphate, glycerin, hydrochloric acid (for pH adjustment), orange flavor, sodium benzoate, sucralose, water, and xanthan gum.

12 CLINICAL PHARMACOLOGY

12.1 Mechanism of Action

Vamorolone is a corticosteroid that acts through the glucocorticoid receptor to exert anti-inflammatory and immunosuppressive effects. The precise mechanism by which vamorolone exerts its effect in patients with DMD is unknown.

12.2 Pharmacodynamics

Vamorolone produced a dose-dependent decrease in morning cortisol levels in the clinical studies. Treatment with corticosteroids is associated with a suppression of endogenous cortisol concentrations and an impairment of the hypothalamus-pituitary-adrenal (HPA) axis function. A dose-dependent increase in leukocyte counts and lymphocyte counts was observed in clinical studies with vamorolone.

Cardiac Electrophysiology

Vamorolone does not cause a mean increase in the QTc interval >20 milliseconds (ms) at 1.6 times the approved recommended dose.

12.3 Pharmacokinetics

The major route of elimination is by metabolism with subsequent excretion of metabolites into urine. The pharmacokinetics (PK) are linear and vamorolone exposure increases proportionally with either single (0.1 to 20 mg/kg) or multiple (0.25 to 20 mg/kg) doses. Vamorolone does not accumulate with repeated administration after once daily dosing.

Absorption

After oral administration with food, the median Tmaxis about 2 hours (range 0.5 to 5 hours).

Effect of Food

Co-administration of vamorolone (2 mg/kg) with a high-fat/high-calorie meal reduced Cmaxby 18%, increased AUC by 13%, and delayed Tmaxby one hour. Co-administration of vamorolone (2 mg/kg) with a low-fat/low-calorie meal reduced Cmaxby 4%, increased AUC by 14%, and delayed Tmaxby one hour [see Dosage and Administration (2.2)].

Distribution

The apparent volume of distribution of vamorolone for a DMD patient with a body weight of 20 kg taking AGAMREE with a meal is 162 L based on the population PK analysis. Protein binding is 88.1% in vitro. The blood to plasma ratio is approximately 0.87.

Elimination

Vamorolone clearance for a DMD patient with a body weight of 20 kg taking AGAMREE with a meal is 58 L/h based on the population PK analysis. The terminal elimination half-life of vamorolone is approximately 2 hours.

Metabolism

Vamorolone is metabolized via multiple Phase I and Phase II metabolic pathways, such as glucuronidation, hydroxylation, and reduction. The main plasma and urine metabolites are formed through direct glucuronidation as well as hydrogenation with subsequent glucuronidation. Metabolism of vamorolone is mediated through CYP3A4/5, CYP2C8, UGT1A3, UGT2B7, and UGT2B17.

Excretion

Approximately 30% of vamorolone dose is excreted in feces (15.4% unchanged) and 48% of vamorolone dose is excreted in urine as metabolites (<1% unchanged). The major metabolites in urine are glucuronides.

Specific Populations

No clinically significant differences in the pharmacokinetics of vamorolone were observed based on race and sex.

Pediatric Patients

In children ages 4 to 7 years (N=12) who were administered 6 mg/kg of AGAMREE daily, on Day 1 and Day 14, the Cmaxvalues (arithmetic mean, SD) of vamorolone were 856 ng/mL (471) and 970 ng/mL (270), respectively, and the AUC24values (arithmetic mean, SD) of vamorolone were 3279 ng·h/mL (1693) and 3606 ng·h/mL (897), respectively. The pharmacokinetics of vamorolone was also characterized in DMD children ages 2 to 4 (N=6). Similar PK parameters were observed in younger children after administration of 6 mg/kg AGAMREE when compared to older children.

Patients with Hepatic Impairment

In a clinical study (N=16), vamorolone Cmaxand AUC0infvalues were increased by approximately 1.7- and 2.6-fold, respectively, in subjects with moderate hepatic impairment (Child-Pugh Class B) compared with healthy matched controls [see Dosage and Administration (2.3) and Use in Specific Populations (8.6)] . There is no experience with vamorolone in patients with severe hepatic impairment.

Drug Interaction Studies

Effect of Strong CYP3A4 Inhibitors on Vamorolone

Compared to administration of vamorolone alone, administration of vamorolone following multiple doses of a strong CYP3A4 inhibitor (itraconazole) increased vamorolone Cmaxand AUC by 8% and 44%, respectively [see Drug Interactions (7.1)]. There is no experience with vamorolone when coadministered with moderate and weak CYP3A4 inhibitors.

In Vitro Studies

Metabolizing Enzymes

Vamorolone induces CYP3A4 in vitro. Other compounds that are substrates of CYP3A4 may have decreased plasma concentrations when co-administered with AGAMREE. However, no clinical drug interaction studies with CYP3A4 substrates were conducted.

Vamorolone does not inhibit CYP or UGT isoenzymes at clinically relevant concentrations.

Transporter Systems

Vamorolone is not an inhibitor of P-gp, BCRP, OATP1B1, OATBP1B3, OCT2, OAT1, OAT3, MATE1, MATE2-K, or BSEP at clinically relevant concentrations. Vamorolone is not a substrate of P-gp, BCRP, OATP1B1, OATBP1B3, OCT2, OAT1, OAT3, MATE1, MATE2-K, or BSEP.

13 NONCLINICAL TOXICOLOGY

13.1 Carcinogenesis, Mutagenesis, Impairment of Fertility

Carcinogenesis

Carcinogenicity studies have not been conducted with vamorolone.

Mutagenesis

Vamorolone was negative for genotoxicity in in vitro (bacterial reverse mutation and cultured mouse lymphocyte chromosomal aberration) and in vivo (mouse micronucleus) assays.

Impairment of Fertility

Fertility studies in animals were not conducted with vamorolone. Oral administration of vamorolone (0, 2, 10, or 50 mg/kg/day) for 39 weeks to dogs resulted in spermatocyte and spermatid degeneration in the testes and oligospermia and germ cell debris in the epididymis in males at the high dose and absence of corpora lutea in the ovaries in females at all doses. Plasma exposures (AUC) in males at the no-effect dose for testicular toxicity (10 mg/kg) was lower than that at the maximum recommended human dose of AGAMREE (300 mg/day).

14 CLINICAL STUDIES

The effectiveness of AGAMREE for the treatment of Duchenne muscular dystrophy (DMD) was evaluated in a multicenter, randomized, double-blind, parallel-group, placebo- and active-controlled, multinational 24-week study (Study 1; NCT03439670). The study randomized 121 male patients with DMD to one of the following treatment groups: AGAMREE 6 mg/kg/day (n=30), AGAMREE 2 mg/kg/day (n=30), prednisone 0.75 mg/kg/day (n=31), or placebo (n=30) for 24 weeks. After 24 weeks, patients on prednisone and placebo received either AGAMREE 6 mg/kg/day (n=29) or AGAMREE 2 mg/kg/day (n=29) for an additional 20 weeks. The study included patients 4 to less than 7 years of age at time of enrollment in the study who were corticosteroid naïve and ambulatory, with a confirmed diagnosis of DMD. At baseline, patients had a mean age of 5.4 years, 83% were Caucasian, 10% were Asian, and 96% were not Hispanic or Latino.

The primary endpoint was the change from baseline to Week 24 in Time to Stand Test (TTSTAND) velocity for AGAMREE 6 mg/kg/day compared to placebo. TTSTAND velocity is a measure of muscle function that measures the time required for the patient to stand to an erect position from a supine position (floor). The key secondary endpoints consisted of change from baseline to Week 24 in TTSTAND velocity (AGAMREE 2 mg/kg/day vs placebo), 6 Minute Walk Test (6MWT) distance (AGAMREE 6 mg/kg/day vs placebo and 2 mg/kg/day vs placebo) and Time to Run/Walk 10 meters (TTRW) velocity (AGAMREE 6 mg/kg/day vs placebo and 2 mg/kg/day vs placebo). The 6MWT measures the distance that a patient can walk on a flat, hard surface in a period of 6 minutes and TTRW measures the time that it takes a patient to run or walk 10 meters. The fixed sequential testing process was applied to the key secondary endpoints in the order listed above.

The primary endpoint and key secondary endpoints were met for the AGAMREE 6 mg/kg/day treatment group. The AGAMREE 2 mg/kg/day treatment group was statistically significant vs. placebo for TTSTAND and 6MWT, but was not statistically significant vs. placebo for TTRW. See Figure 1and Table 2for efficacy results from Week 24.

Figure 1: Least-Squares Mean Change in Time to Stand (TTSTAND) Velocity (rises/sec)

Table 2: Change from Baseline to Week 24 on TTSTAND, 6MWT, and TTRW Compared to Placebo
Parameter | Placebo | AGAMREE 2 mg/kg/d | AGAMREE 6 mg/kg/d
TTSTAND velocity (rises/sec) Baseline Mean change from baseline Difference from placebo (95% CI) p-value | 0.200 -0.012 N/A N/A | 0.184 0.033 0.045 (0.008, 0.082) 0.017 | 0.186 0.048 0.060 (0.023, 0.098) 0.002*
6MWT distance (meters) Baseline Mean change from baseline Difference from placebo (95% CI) p-value | 355 -14 N/A N/A | 316 27 40 (13, 68) 0.004 | 313 29 42 (16, 69) 0.002
TTRW velocity (meters/sec) Baseline Mean change from baseline Difference from placebo (95% CI) p-value | 1.735 0.014 N/A N/A | 1.563 0.141 0.127 (-0.026, 0.281) 0.103 | 1.600 0.258 0.244 (0.093, 0.395) 0.002
Baseline values are presented with descriptive statistics (mean). Mean changes and differences are model-based least-squares means and mean differences. Positive numbers indicate improvement as compared with the baseline value.
*Primary endpoint

16 HOW SUPPLIED/STORAGE AND HANDLING

16.1 How Supplied

AGAMREE oral suspension is an orange flavored homogeneous white to off-white suspension, containing 40 mg/mL of vamorolone.

AGAMREE is supplied as 100 mL in 125 mL glass bottle packaged with one bottle adapter, two 5 mL oral syringes, and an Instructions for Use: NDC 69616-264-38.

16.2 Storage and Handling

Store the bottle upright at room temperature between 20°C to 25°C (68°F to 77°F). Excursions permitted between 15°C to 30°C (59°F to 86°F) in the original carton. See USP controlled room temperature.

After opening, store the bottle upright in a refrigerator 2°C to 8°C (36°F to 46°F). Do not freeze.

Discard any unused AGAMREE oral suspension remaining after 3 months of first opening the bottle.

17 PATIENT COUNSELING INFORMATION

Advise the patients and/or caregivers to read the FDA-approved patient labeling (Instructions for Use).

Administration

- Warn patients and/or caregivers to not stop taking AGAMREE abruptly or without first checking with their healthcare providers as there may be a need for gradual dose reductions to decrease the risk of adrenal insufficiency crisis [see Dosage and Administration (2.7) and Warnings and Precautions (5.1)].
- AGAMREE oral suspension should be taken once daily, preferably with a meal.
- AGAMREE oral suspension must be shaken well for about 30 seconds prior to measuring out each dose with the enclosed oral syringe.
- Discard any unused AGAMREE oral suspension remaining after 3 months of first opening the bottle.

Immunosuppression and Increased Risk of Infection

Tell patients and/or caregivers to inform their healthcare provider if the patient has had recent or ongoing infections or if they have recently received a vaccine. Medical advice should be sought immediately if the patient develops fever or other signs of infection. Patients and/or caregivers should be made aware that some infections can potentially be severe and fatal.

Warn patients who are on corticosteroids to avoid exposure to chickenpox or measles and to alert their healthcare provider immediately if they are exposed [see Warnings and Precautions (5.2)] .

Alterations in Cardiovascular/Renal Function

Inform patients and/or caregivers that corticosteroids, including AGAMREE, can cause an increase in blood pressure and water retention. If this occurs, dietary salt restriction and potassium supplementation may be needed [see Warnings and Precautions (5.3)].

Behavioral and Mood Disturbances

Advise patients and/or caregivers about the potential for severe behavioral and mood changes with AGAMREE and encourage them to seek medical attention if psychiatric symptoms develop [see Warnings and Precautions (5.5)].

Decreases in Bone Mineral Density

Advise patients and/or caregivers about the risk of osteoporosis with prolonged use of AGAMREE, which can predispose the patient to vertebral and long bone fractures [see Warnings and Precautions (5.6)].

Ophthalmic Effects

Inform patients and/or caregivers that AGAMREE may cause cataracts or glaucoma and advise monitoring if administered for more than 6 weeks [see Warnings and Precautions (5.7)].

Vaccination

Advise patients and/or caregivers to bring immunizations up-to-date according to immunization guidelines prior to starting therapy with AGAMREE. Live-attenuated or live vaccines should be administered at least 4 to 6 weeks prior to starting AGAMREE. Inform patients and/or caregivers that they may receive concurrent vaccinations with use of AGAMREE, except for live-attenuated or live vaccines [see Warnings and Precautions (5.8)].

Drug Interactions

Certain medications can cause an interaction with AGAMREE [see Drug Interactions (7.1)] . Advise patients and/or caregivers to inform their healthcare provider of all the medicines the patient is taking, including over-the-counter medicines (such as insulin, aspirin or other NSAIDS), dietary supplements, and herbal products. Inform patients and/or caregivers that alternate therapy, dosage adjustment, and/or special test(s) may be needed during the treatment.

Manufactured for:
Catalyst Pharmaceuticals, Inc.
Coral Gables, FL 33134, USA

AGAMREE Oral Suspension made in Italy.

AGAMREE®is a registered trademark of Santhera Pharmaceuticals (Schweiz) AG.

6010 Rev. B.

Instructions for Use

AGAMREE® (ah gam' ree)
(vamorolone)
40 mg/mL oral suspension

Read this Instructions for Use before you start using AGAMREE oral suspension and each time you get a new bottle.
This information does not take the place of talking to your healthcare provider about your medical condition or treatment.

Supplies provided in the AGAMREE carton:

- 1 bottle containing 100 mL of AGAMREE, with a child-resistant cap
- 1 bottle adapter
- Two 5 mL oral syringes
- 1 Prescribing information with Instructions for Use

Important information you need to know before taking AGAMREE:

- For oral use only(take by mouth).
- Always use the oral syringes provided with your AGAMREE oral suspension to make sure you measure the right amount.
- Ask your healthcare provider or pharmacist to show you how to measure your prescribed daily dose using the oral syringe.
- Call your pharmacist if your oral syringes are lost or damaged.
- Each oral syringe can be used for 45 days. Call your pharmacist if you need more oral syringes.
- Take AGAMREE exactly as your healthcare provider tells you to take it. Do notstop taking AGAMREE suddenly without first speaking with your healthcare provider.
- AGAMREE oral suspension should be taken 1-time daily with a meal.
- Do notmix the AGAMREE oral suspension with any type of liquids before taking or giving the prescribed daily dose.
- Do notuse AGAMREE 3 months after opening the bottle. Write the date of first opening on your AGAMREE bottle when you first open it.

Storing AGAMREE

- Store the unopened bottle upright at room temperature between 68°F to 77°F (20°C to 25°C) in the original carton. After opening the bottle, store the bottle upright in a refrigerator between 36°F to 46°F (2°C to 8°C).
- Do notfreeze.
- Throw away (discard) any unused AGAMREE oral suspension remaining after 3 months of first opening the bottle.

Keep AGAMREE oral suspension and all medicines out of the reach of children.

Preparing the AGAMREE bottle
Step 1 | Place the child-resistant bottle cap on the bottle. Make sure the child-resistant bottle cap is tightly secured and shake the bottle well for about 30 seconds.
Step 2 | Open the bottle by firmly pressing down on the child-resistant bottle cap and turning it to the left (counter-clockwise). Do notthrow away the child-resistant bottle cap.
Step 3 | Place the open bottle on a flat surface. Firmly insert the bottle adapter into the bottle by pushing it tightly into the top of the bottle. The top edge of the bottle adapter should be even with the bottle top. Do notremove the bottle adapter after it is inserted into the bottle. Write the date of first opening on your AGAMREE bottle when you first open it.
Preparing and withdrawing the AGAMREE dose
Step 4 | Check your dose in millilitres (mL) as prescribed by your healthcare provider. Each mark on the oral syringe is equal to 0.1 mL. Do nottake more than the prescribed daily dose.
Step 5 | Place the bottle on a flat surface. Before inserting the tip of the oral syringe into the bottle adapter, push the plunger completely down toward the tip of the oral syringe. Use 1 hand to hold the bottle upright. Insert the oral syringe tip firmly into the opening of the bottle adapter.
Step 6 | Hold the oral syringe in place and carefully turn the bottle upside down. Pull the plunger down slowly until you reach the mL markings on the plunger for the prescribed dose. Do notpull the plunger out of the oral dispenser.
Step 7 | If there are large bubbles in the oral syringe or if you draw up the wrong dose of AGAMREE, push the plunger all the way up so that AGAMREE flows back into the bottle. Pull the plunger down slowly until you reach the mL markings for your prescribed dose. Repeat Step 7if any large air bubbles remain or if you draw up the wrong dose of AGAMREE.
Step 8 | Leave the tip of the oral syringe in the bottle and turn the entire bottle to an upright position. Slowly remove the oral syringe tip from the bottle by pulling the oral syringe straight up. Do nothold the oral syringe by the plunger, because the plunger may come out. Take or give AGAMREE right away after it is drawn up into the oral syringe. Do notstore the filled oral syringe.
Taking AGAMREE
Step 9 | The child or adult should sit upright to take a dose of AGAMREE. Place the oral syringe tip in the mouth towards the cheek and slowly push the plunger down until the oral syringe is empty. Do notforcefully push on the plunger. Do notgive AGAMREE too fast into the back of the mouth or throat. This may cause choking.
Step 10 | If your prescribed dose is greater than 5 mL, repeat Steps 4 to 9.
After taking or giving AGAMREE
Step 11 | Put the child-resistant bottle cap back on the bottle and turn the cap to the right (clockwise) to close the bottle. Keep the bottle tightly closed after each use.
Cleaning the oral syringes
Step 12 | Remove the plunger from the barrel of the oral syringe. Rinse the barrel and plunger with running warm water only and let them air dry on a paper towel. When the oral syringe and plunger are dry, put the plunger back in the oral syringe for the next dose. Store the oral syringe in a clean, dry place.

For further information call 1-833-422-8259 or go to www.YourCatalystPathways.com.

Manufactured for: Catalyst Pharmaceuticals, Inc., Coral Gables, FL 33134

This Instructions for Use has been approved by the U.S. Food and Drug Administration.

Revised: 03/2024

Principal Display Panel – 100 mL Carton Label

NDC 69616-264-38

100 mL

AGAMREE®
(vamorolone)

Oral suspension

Rx only

40 mg/mL

For Oral Administration Only

Catalyst Pharmaceuticals, Inc.

Principal Display Panel – 100 mL Carton Label

NDC 69616-265-38

100 mL

AGAMREE®
(vamorolone)

Oral suspension

Rx only

40 mg/mL

For Oral Administration Only

Date of first Opening:

_______ / ______ / _______